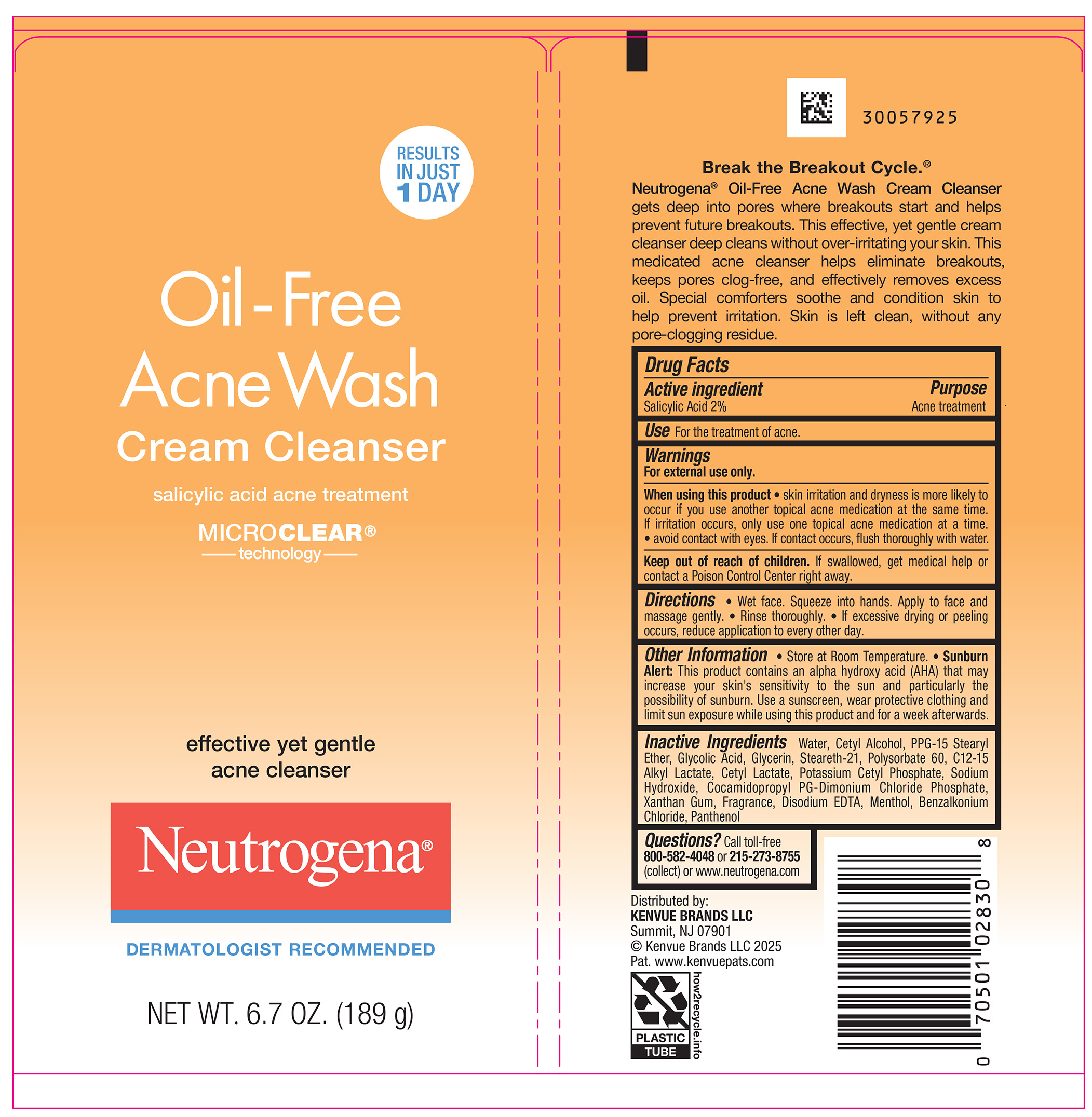 DRUG LABEL: Neutrogena Oil-Free Acne Wash Cream Cleanser
NDC: 69968-0940 | Form: CREAM
Manufacturer: Kenvue Brands LLC
Category: otc | Type: HUMAN OTC DRUG LABEL
Date: 20250818

ACTIVE INGREDIENTS: SALICYLIC ACID 20 mg/1 g
INACTIVE INGREDIENTS: BENZALKONIUM CHLORIDE; WATER; EDETATE DISODIUM; CETYL ALCOHOL; POTASSIUM CETYL PHOSPHATE; CETYL LACTATE; POLYSORBATE 60; XANTHAN GUM; COCAMIDOPROPYL PG-DIMONIUM CHLORIDE PHOSPHATE; MENTHOL; C12-15 ALKYL LACTATE; PPG-15 STEARYL ETHER; GLYCOLIC ACID; GLYCERIN; STEARETH-21; SODIUM HYDROXIDE; PANTHENOL

Neutrogena Oil-Free Acne Wash Cream Cleanser

Drug Facts

Active ingredient

Salicylic Acid 2%

Purpose

Acne treatment

Use

For the treatment of acne.

Warnings

For external use only.

▪ When using this product

▪ Skin irritation and dryness is more likely to occur if you use another topical acne medication at the same time. If irritation occurs, only use one topical acne medication at a time.

▪ avoid contact with eyes. If contact occurs, flush thoroughly with water.

▪ Keep out of reach of children. If swallowed, get medical help or contact a Poison Control Center right away.

Directions

• Wet face. Squeeze into hands. Apply to face and massage gently.

• Rinse thoroughly.

• If excessive drying or peeling occurs, reduce application to every other day.

Other information

• Store at Room Temperature.

• Sunburn Alert: This product contains an alpha hydroxy acid (AHA) that may increase your skin's sensitivity to the sun and particularly the possibility of sunburn. Use a sunscreen, wear protective clothing and limit sun exposure while using this product and for a week afterwards.

Inactive ingredients

Water, Cetyl Alcohol, PPG-15 Stearyl Ether, Glycolic Acid, Glycerin, Steareth-21, Polysorbate 60, C12-15 Alkyl Lactate, Cetyl Lactate, Potassium Cetyl Phosphate, Sodium Hydroxide, Cocamidopropyl PG-Dimonium Chloride Phosphate, Xanthan Gum, Fragrance, Disodium EDTA, Menthol, Benzalkonium Chloride, Panthenol

Questions?

Call toll-free 800-582-4048 or 215-273-8755 (collect) or www.neutrogena.com

Distributed by:
Kenvue brands LLC

Summit, NJ 07901

PRINCIPAL DISPLAY PANEL - 189 g Tube Label

RESULTS

IN JUST

1 DAY

Oil - Free

Acne Wash

Cream Cleanser

salicylic acid acne treatment

MICRO CLEAR®

Technology

effective yet gentle

acne cleanser

Neutrogena®

DERMATOLOGIST RECOMMENDED

NET WT. 6.7 OZ. (189 g)